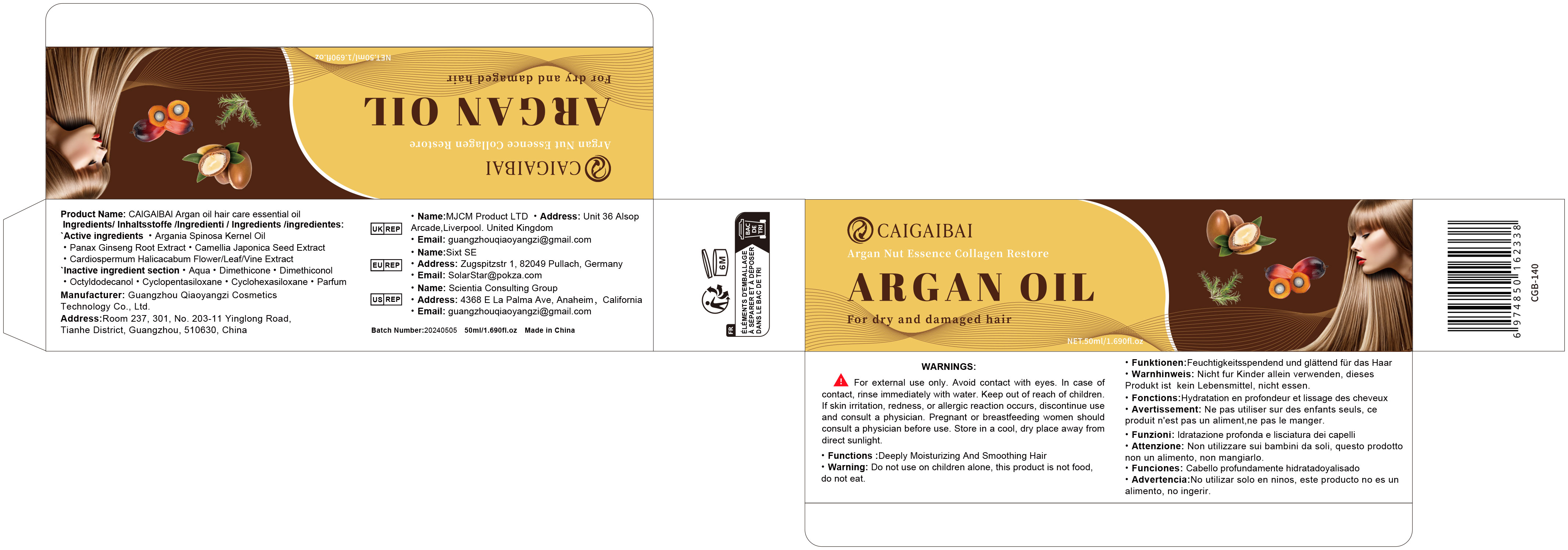 DRUG LABEL: Argan oil hair care essential oil
NDC: 84751-139 | Form: OIL
Manufacturer: Guangzhou Qiaoyangzi Cosmetics Technology Co Ltd
Category: otc | Type: HUMAN OTC DRUG LABEL
Date: 20241030

ACTIVE INGREDIENTS: ARGAN OIL 2.5 mg/50 mL; ASIAN GINSENG 1.1 mg/50 mL; CARDIOSPERMUM HALICACABUM FLOWERING TOP 0.35 mg/50 mL; CAMELLIA JAPONICA SEED 0.55 mg/50 mL
INACTIVE INGREDIENTS: AQUA 55.85 mg/50 mL

Purpose

Effectively reduces hair loss and promotes hair growth.
Provides deep hydration and nourishment, enhancing hair shine.
Improves scalp health and alleviates scalp irritation.
Increases hair elasticity and resistance to breakage.

Uses

INDICATIONS & USAGE:
Suitable for adults seeking to reduce hair loss and promote hair growth.
Suitable for all hair types, especially weak, brittle, or thinning hair.
Directions for use: Apply a suitable amount of oil (about one to two pumps) evenly to the scalp and dry hair, gently massaging to enhance absorption. Can be used once daily or adjusted based on hair condition as needed.

Warnings

For external use only. Avoid contact with eyes. In case of contact, rinse immediately with water.
Keep out of reach of children.
If skin irritation, redness, or allergic reaction occurs, discontinue use and consult a physician.
Pregnant or breastfeeding women should consult a physician before use.
Store in a cool, dry place away from direct sunlight.

Stop use

Discontinue use and consult a physician if any skin irritation, redness, itching, or allergic reaction occurs.

Do not use

If you are allergic to any of the ingredients.
On broken, inflamed, or irritated skin.
In conjunction with other hair loss treatments.

Keep out of reach of children!

Precautions for Use

WHEN USING:
A slight tingling sensation may occur, but it is usually temporary.
Avoid applying the product directly to the inner eyelid or lash line.
If discomfort or irritation occurs while using the product, discontinue use immediately.

Instructions for Use

Cleanse the scalp and hair to ensure they are free from oil and dirt.
Dispense a suitable amount of oil (about one to two pumps) into your palm.
Apply evenly to the scalp and dry hair, gently massaging to enhance absorption.
Optionally, use a hairdryer to warm the product for better effectiveness.
Recommended for use once daily, in the morning or evening.

DOSAGE & ADMINISTRATION SECTION

DOSAGE & ADMINISTRATION:
Use approximately one to two pumps of oil per application.
Apply evenly to dry scalp and hair, gently massaging to enhance absorption.
Frequency can be adjusted as needed, but daily use is recommended for best results.

Active ingredients

Argania Spinosa Kernel Oil 2.50%
Panax Ginseng Root Extract 1.10%
Camellia Japonica Seed Extract 0.55%
Cardiospermum Halicacabum Flower/Leaf/Vine Extract 0.35%

INACTIVE INGREDIENT SECTION

Aqua 55.85%
Dimethicone 15.00%
Dimethiconol 9.00%
Octyldodecanol 7.00%
Cyclopentasiloxane 5.00%
Cyclohexasiloxane 3.50%
Parfum 0.15%